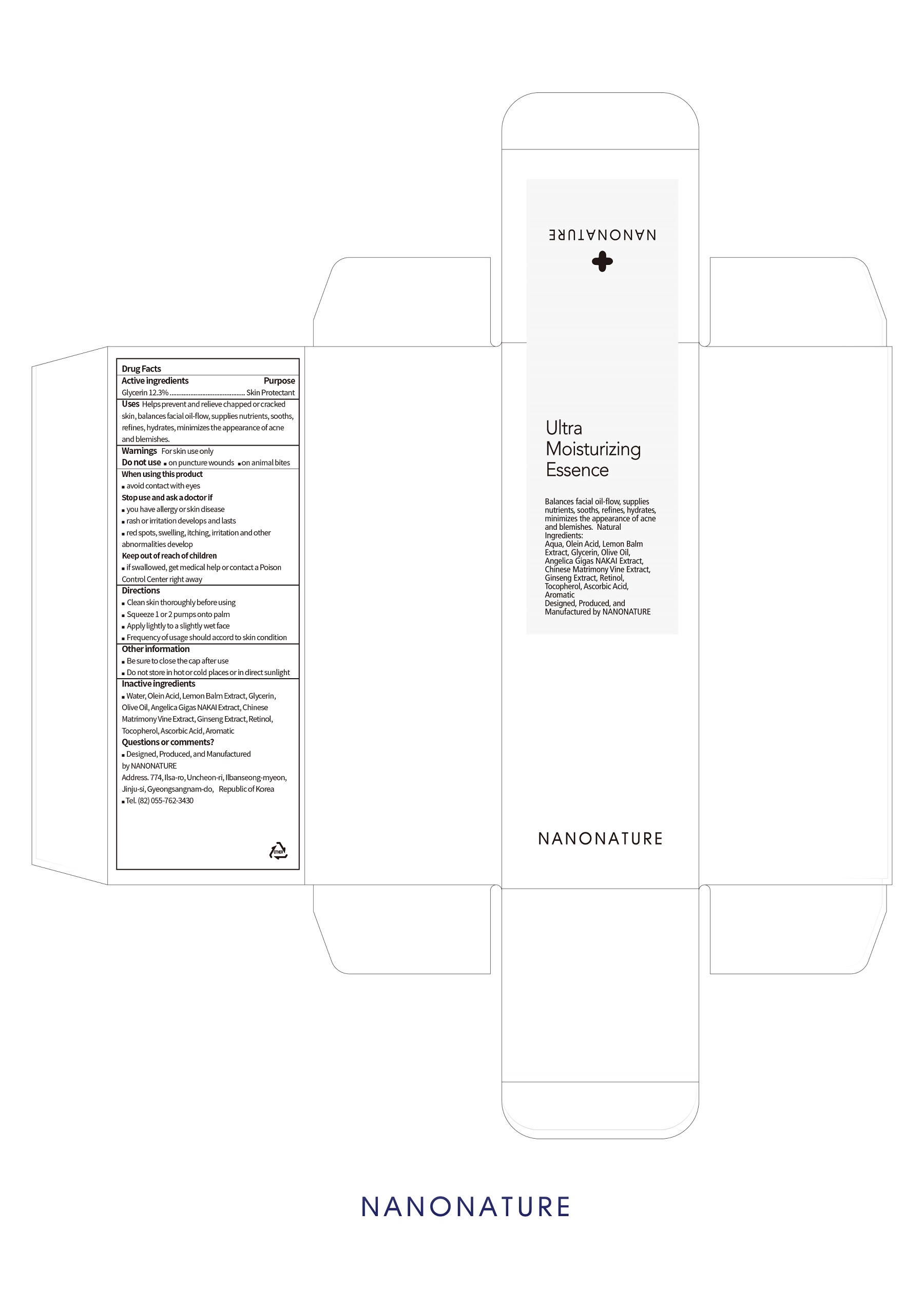 DRUG LABEL: Ultra Moisturizing Essence
NDC: 71538-002 | Form: SOLUTION
Manufacturer: NANONATURE
Category: otc | Type: HUMAN OTC DRUG LABEL
Date: 20170717

ACTIVE INGREDIENTS: Glycerin 12.3 g/100 mL
INACTIVE INGREDIENTS: Water; Olive Oil; Tocopherol; Retinol

ACTIVE INGREDIENT

Glycerin (12.3%) - Skin Protectant

INACTIVE INGREDIENT

Water, Olein Acid, Lemon Balm Extract, Olive Oil, Angelica Gigas NAKAI Extract, Chinese Matrimony Vine Extract, Ginseng Extract, Retinol, Tocopherol, Ascobic Acid, Aromatic

PURPOSE

Skin Protectant

WARNINGS

For skin use only.
Do not use
 on puncture wounds  on animal bites
When using this product
 avoid contact with eyes
Stop use and ask a doctor if
 you have allergy or skin disease
 rash or irritation develops and lasts
 red spots, swelling, itching, irritation and other abnormalities developsFor skin use only.
Do not use
 on puncture wounds  on animal bites
When using this product
 avoid contact with eyes
Stop use and ask a doctor if
 you have allergy or skin disease
 rash or irritation develops and lasts
 red spots, swelling, itching, irritation and other abnormalities develops

KEEP OUT OF REACH OF CHILDREN

 if swallowed, get medical help or contact a Poison Control Center right away

INDICATIONS & USAGE

 Clean skin thoroughly before using
 Squeeze 1 or 2 pumps onto palm
 Apply lightly to a slightly wet face
 Frequency of usage should accord to skin condition

DOSAGE & ADMINISTRATION

 Clean skin thoroughly before using
 Squeeze 1 or 2 pumps onto palm
 Apply lightly to a slightly wet face
 Frequency of usage should accord to skin condition